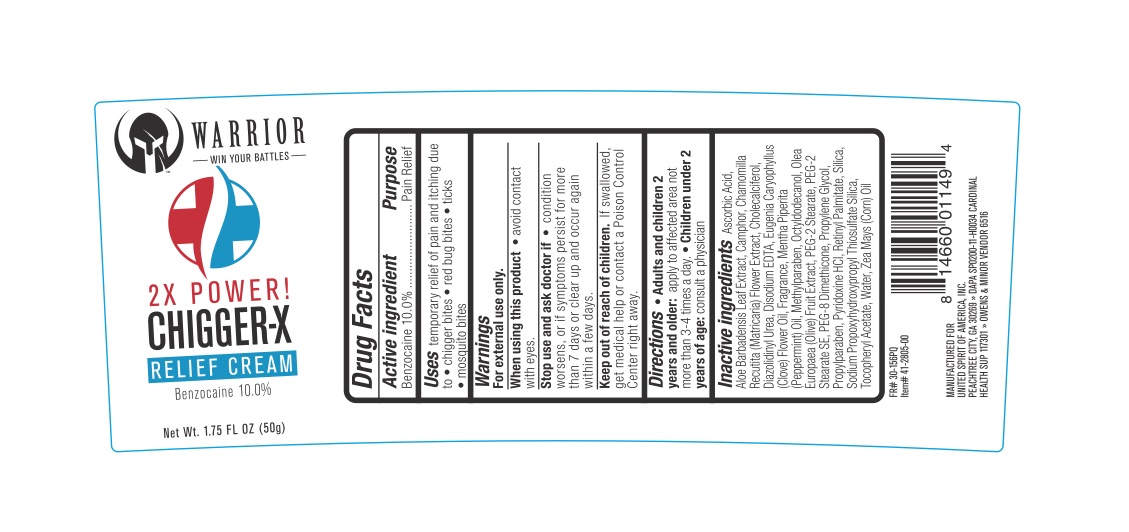 DRUG LABEL: Warrior Chiggerex Relief
NDC: 72839-069 | Form: CREAM
Manufacturer: Derma Care Research Labs, LLC
Category: otc | Type: HUMAN OTC DRUG LABEL
Date: 20241215

ACTIVE INGREDIENTS: BENZOCAINE 10 g/100 g
INACTIVE INGREDIENTS: CAMPHOR (SYNTHETIC); PEG-2 STEARATE; CLOVE OIL; MATRICARIA CHAMOMILLA FLOWERING TOP OIL; PROPYLENE GLYCOL; OCTYLDODECANOL; SODIUM PROPOXYHYDROXYPROPYL THIOSULFATE SILICA; SILICON DIOXIDE; PEPPERMINT OIL; .ALPHA.-TOCOPHEROL ACETATE; VITAMIN A PALMITATE; ALOE VERA LEAF; DIAZOLIDINYL UREA; 4-DESOXYPYRIDOXINE HYDROCHLORIDE; EDETATE DISODIUM; CORN OIL; ASCORBIC ACID; OLIVE OIL; METHYLPARABEN; PEG-8 DIMETHICONE; WATER; CHOLECALCIFEROL

Warrior Chiggerex

ACTIVE INGREDIENT

Benzocaine 10%

PURPOSE

Pain Relief

DOSAGE AND ADMINISTRATION

Uses: for the temporary relief of pain and itching associated with chigger bites, red bug bites, ticks, and mosquito bites.

WARNINGS

For external use only.

When using this product avoid contact with eyes. Stop use and ask a doctor if the condition worsens, symptoms persist for more than 7 days or clear up and occur again within a few days.

KEEP OUT OF REACH OF CHILDREN

In case of accidental ingestion, seek professional assistance or contact a Poison Control Center immediately.

INDICATIONS AND USAGE

Adults and children 2 years and older: apply to the affected area, not more than 3 to 4 times daily. Children under 2 years of age: ask a doctor.

INACTIVE INGREDIENT

Ascorbic Acid, Aloe Barbadensis Leaf Extract, Camphor, Chamomilla Recutita (Matricaria) Flower Extract, Cholecalciferol, Diazolidinyl Urea, Disodium EDTA, Eugenia Caryophyllus (Clove) Flower Oil, Fragrance, Mentha Piperita (Peppermint) Oil, Methylparaben, Octyldodecanol, Olea Europaea (Olive) Fruit Extract, PEG-2 Stearate, PEG-2 Stearate SE, PEG-8 Dimethicone, Propylene Glycol, Propylparaben, Pyridoxine HCl, Retinyl Palmitate, Silica, Sodium Propoxyhydroxypropyl Thiosulfate Silica, Tocopheryl Acetate, Water, Zea Mays (Corn) Oil.